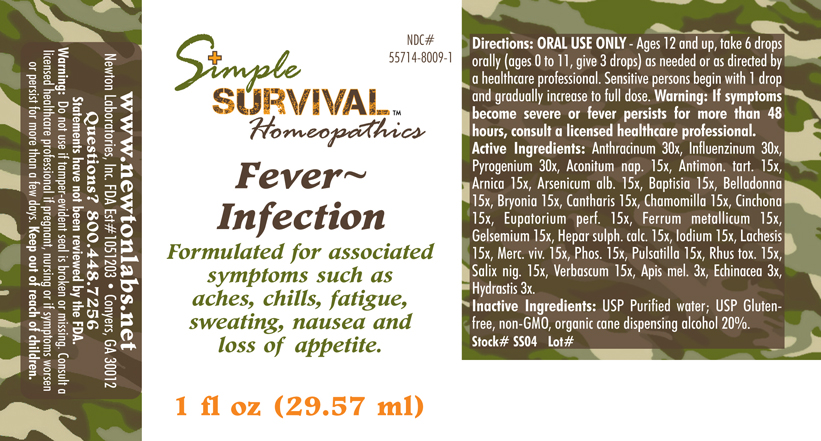 DRUG LABEL: Fever - Infection 
NDC: 55714-8009 | Form: LIQUID
Manufacturer: Newton Laboratories, Inc.
Category: homeopathic | Type: HUMAN OTC DRUG LABEL
Date: 20140415

ACTIVE INGREDIENTS: Bacillus Anthracis Immunoserum Rabbit 30 [hp_X]/1 mL; Influenza A Virus 30 [hp_X]/1 mL; Rancid Beef 30 [hp_X]/1 mL; Aconitum Napellus 15 [hp_X]/1 mL; Antimony Potassium Tartrate 15 [hp_X]/1 mL; Arnica Montana 15 [hp_X]/1 mL; Arsenic Trioxide 15 [hp_X]/1 mL; Baptisia Tinctoria 15 [hp_X]/1 mL; Atropa Belladonna 15 [hp_X]/1 mL; Bryonia Alba Root 15 [hp_X]/1 mL; Lytta Vesicatoria 15 [hp_X]/1 mL; Matricaria Recutita 15 [hp_X]/1 mL; Cinchona Officinalis Bark 15 [hp_X]/1 mL; Eupatorium Perfoliatum Flowering Top 15 [hp_X]/1 mL; Iron 15 [hp_X]/1 mL; Gelsemium Sempervirens Root 15 [hp_X]/1 mL; Calcium Sulfide 15 [hp_X]/1 mL; Iodine 15 [hp_X]/1 mL; Lachesis Muta Venom 15 [hp_X]/1 mL; Mercury 15 [hp_X]/1 mL; Phosphorus 15 [hp_X]/1 mL; Pulsatilla Vulgaris 15 [hp_X]/1 mL; Toxicodendron Pubescens Leaf 15 [hp_X]/1 mL; Salix Nigra Bark 15 [hp_X]/1 mL; Verbascum Thapsus 15 [hp_X]/1 mL; Apis Mellifera 3 [hp_X]/1 mL; Echinacea, Unspecified 3 [hp_X]/1 mL; Goldenseal 3 [hp_X]/1 mL; Influenza B Virus 30 [hp_X]/1 mL
INACTIVE INGREDIENTS: Alcohol

Fever - Infection

INDICATIONS & USAGE SECTION

Fever - Infection Formulated for associated symptoms such as aches, chills, fatigue, sweating, nausea and loss of appetite.

DOSAGE & ADMINISTRATION SECTION

Directions: ORAL USE ONLY - Ages 12 and up, take 6 drops orally (ages 0 to 11, give 3 drops) as needed or as directed by a healthcare professional. Sensitive persons begin with 1 drop and gradually increase to full dose. Warning: If symptoms become severe or fever persists for more than 48 hours, consult a licensed healthcare professional.

OTC - ACTIVE INGREDIENT SECTION

Anthracinum 30x, Influenzinum 30x, Pyrogenium 30x, Aconitum nap. 15x, Antimon. tart. 15x, Arnica 15x, Arsenicum alb. 15x, Baptisia 15x, Belladonna 15x, Bryonia 15x, Cantharis 15x, Chamomilla 15x, Cinchona 15x, Eupatorium perf. 15x, Ferrum metallicum 15x, Gelsemium 15x, Hepar sulph.calc. 15x, Iodium 15x, Lachesis 15x, Merc. viv. 15x, Phos. 15x, Pulsatilla 15x, Rhus tox. 15x, Salix nig. 15x, Verbascum 15x, Apis mel. 3x, Echinacea 3x, Hydrastis 3x.

OTC - PURPOSE SECTION

Formulated for associated symptoms such as aches, chills, fatigue, sweating, nausea and loss of appetite

INACTIVE INGREDIENT SECTION

Inactive Ingredients: USP Purified Water; USP Gluten-free, non-GMO, organic cane dispensing alcohol 20%.

QUESTIONS SECTION

www.newtonlabs.net Newton Laboratories, Inc. FDA Est # 1051203 - Conyers, GA 30012
Questions? 1.800.448.7256

WARNINGS SECTION

Warning: Do not use if tamper - evident seal is broken or missing. Consult a licensed healthcare professional if pregnant, nursing or if symptoms worsen or persist for more than a few days. Keep out of reach of children.

OTC - PREGNANCY OR BREAST FEEDING SECTION

Consult a licensed healthcare professional if pregnant, nursing or if symptoms worsen or persist for more than a few days.

OTC - KEEP OUT OF REACH OF CHILDREN SECTION

Keep out of reach of children.